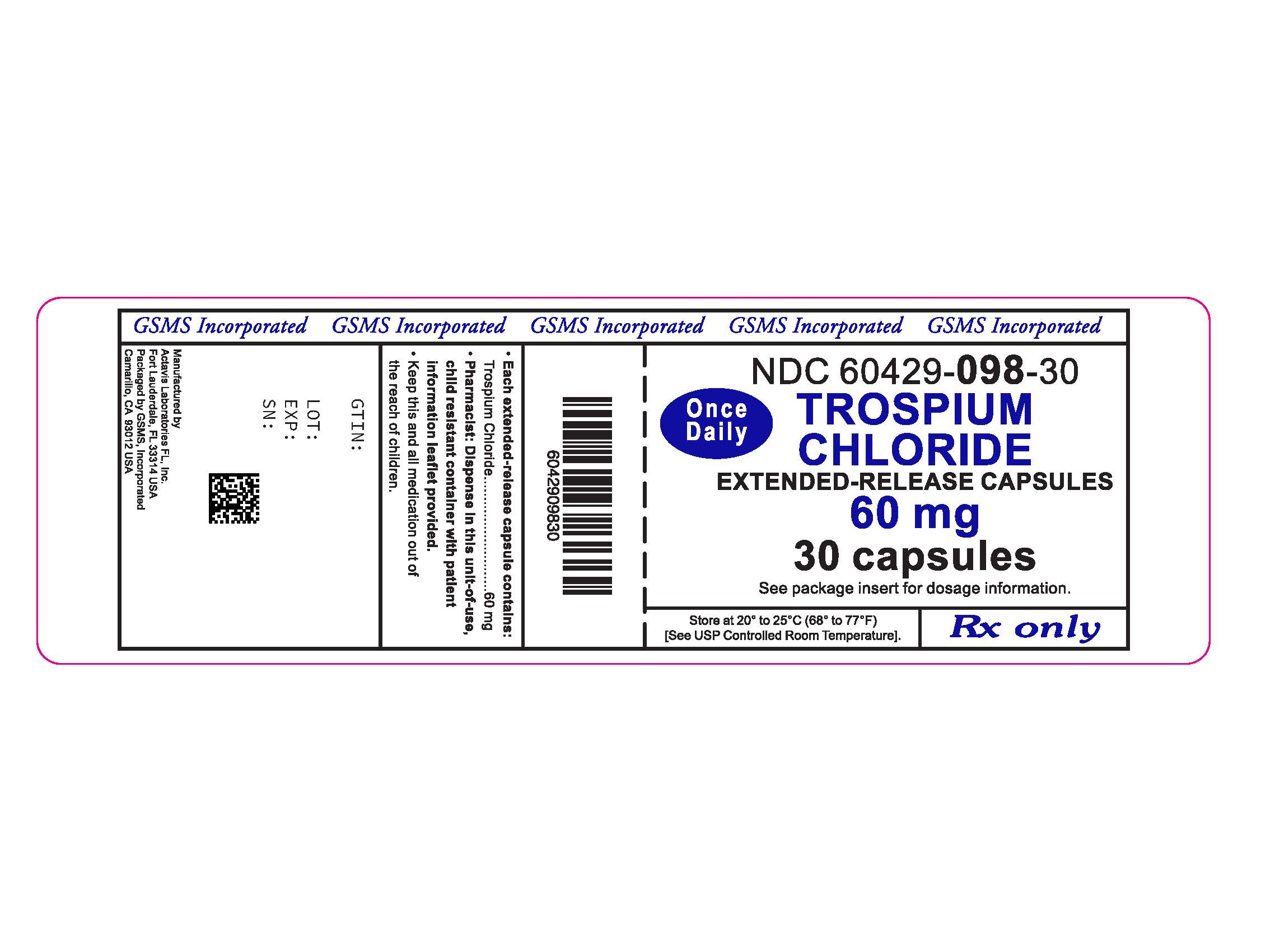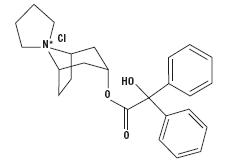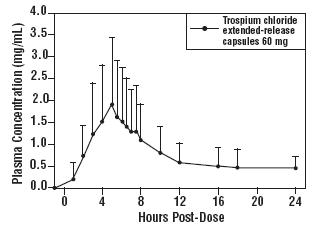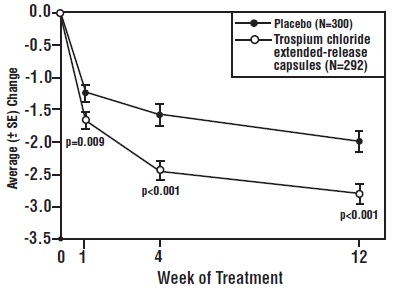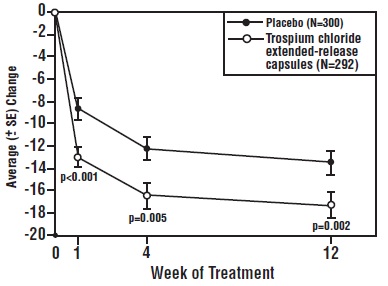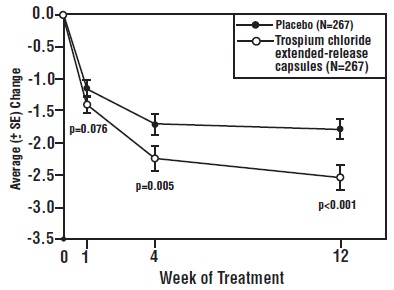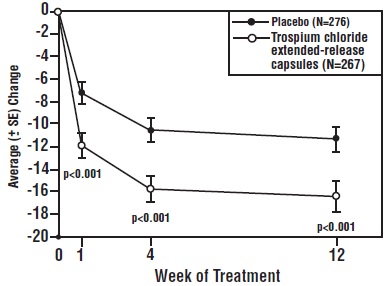 DRUG LABEL: Trospium Chloride
NDC: 60429-098 | Form: CAPSULE, EXTENDED RELEASE
Manufacturer: Golden State Medical Supply, Inc.
Category: prescription | Type: HUMAN PRESCRIPTION DRUG LABEL
Date: 20251211

ACTIVE INGREDIENTS: TROSPIUM CHLORIDE 60 mg/1 1
INACTIVE INGREDIENTS: HYPROMELLOSE 2910 (6 MPA.S); POLYETHYLENE GLYCOL 400; POLY(METHYL ACRYLATE-CO-METHYL METHACRYLATE-CO-METHACRYLIC ACID 7:3:1; 280000 MW); STARCH, CORN; ETHYLCELLULOSE (10 MPA.S); HYPROMELLOSE 2910 (3 MPA.S); POLYETHYLENE GLYCOL 4000; POLYSORBATE 80; POLYVINYL ALCOHOL, UNSPECIFIED; SODIUM LAURYL SULFATE; SUCROSE; TALC; TITANIUM DIOXIDE; TRIETHYL CITRATE; D&C RED NO. 28; D&C YELLOW NO. 10; FD&C BLUE NO. 1; FD&C BLUE NO. 2; FD&C RED NO. 40; FERRIC OXIDE YELLOW; GELATIN; FERROSOFERRIC OXIDE; PROPYLENE GLYCOL; SHELLAC

HIGHLIGHTS OF PRESCRIBING INFORMATION

TROSPIUM CHLORIDE capsule, extended release. These highlights do not include all the information needed to use Trospium Chloride Extended-release Capsules safely and effectively. See full prescribing information for Trospium Chloride Extended-release Capsules.
TROSPIUM CHLORIDE Extended-release Capsules
Initial U.S. Approval: 2004

1 INDICATIONS AND USAGE

Trospium Chloride Extended-release Capsules are a muscarinic antagonist indicated for the treatment of overactive bladder (OAB) with symptoms of urge urinary incontinence, urgency, and urinary frequency. (1)

2 DOSAGE AND ADMINISTRATION

- The recommended dosage of Trospium Chloride Extended-release Capsules is one 60 mg capsule daily in the morning. Trospium Chloride Extended-release Capsules should be dosed with water on an empty stomach, at least one hour before a meal. (2)
- Trospium Chloride Extended-release Capsules are not recommended for use in patients with severe renal impairment (creatinine clearance less than 30 mL/minute). (2)

3 DOSAGE FORMS AND STRENGTHS

- 60 mg capsules (3)

4 CONTRAINDICATIONS

Trospium Chloride Extended-release Capsules are contraindicated in

- patients with urinary retention, gastric retention, or uncontrolled narrow-angle glaucoma, and in patients who are at risk for these conditions (4)
- patients with known hypersensitivity (4)

5 WARNINGS AND PRECAUTIONS

- Trospium Chloride Extended-release Capsules should be administered with caution to patients with clinically significant bladder outflow obstruction or gastrointestinal obstructive disorders due to risk of urinary or gastric retention. (5.1, 5.3)
- Angioedema of the face, lips, tongue and/or larynx has been reported with trospium chloride (5.2)
- In patients with narrow angle glaucoma, Trospium Chloride Extended-release Capsules should be used only with careful monitoring. (5.4)
- Central Nervous System Effects: Somnolence has been reported with Trospium Chloride Extended-release Capsules. Advise patients not to drive or operate heavy machinery until they know how Trospium Chloride Extended-release Capsules affect them. (5.5)
- Trospium Chloride Extended-release Capsules are not recommended for use in patients with severe renal impairment (creatinine clearance less than 30 mL/minute). (5.6)
- Alcohol should not be consumed within 2 hours of Trospium Chloride Extended-release Capsules administration. (5.7)

6 ADVERSE REACTIONS

The most common adverse reactions (greater than or equal to 1 %) with Trospium Chloride Extended-release Capsules are dry mouth (10.7%) and constipation (8.5%). (6.1)

To report SUSPECTED ADVERSE REACTIONS, contact Actavis at 1-800-272-5525 or FDA at 1-800-FDA-1088 or www.fda.gov/medwatch.

7 DRUG INTERACTIONS

- Some drugs which are actively secreted by the kidney may interact with trospium by competing for renal tubular secretion. (7)
- Concomitant use with digoxin did not affect the pharmacokinetics of either drug. (7.1)
- Exposure to trospium on average was comparable in the presence of and without antacid, however, some individuals demonstrated increases or decreases in trospium exposure in the presence of antacid. The clinical relevance of these findings is not known. (7.2)
- Concomitant use with metformin immediate release tablets reduced exposure and peak concentration of trospium. (7.3)

8 USE IN SPECIFIC POPULATIONS

- The safety and effectiveness of trospium chloride extended-release capsules in pediatric patients have not been established. (8.4)

FULL PRESCRIBING INFORMATION

1 INDICATIONS AND USAGE

Trospium chloride extended-release capsules are a muscarinic antagonist indicated for the treatment of overactive bladder (OAB) with symptoms of urge urinary incontinence, urgency, and urinary frequency.

2 DOSAGE AND ADMINISTRATION

The recommended dosage of trospium chloride extended-release capsules is one 60 mg capsule daily in the morning. Trospium chloride extended-release capsules should be dosed with water on an empty stomach, at least one hour before a meal.

Trospium chloride extended-release capsules are not recommended for use in patients with severe renal impairment (creatinine clearance less than 30 mL/minute) [see Warnings and Precautions (5.6), Use in Specific Populations (8.6), and Clinical Pharmacology (12.3)].

3 DOSAGE FORMS AND STRENGTHS

Trospium chloride extended-release capsules are supplied as 60 mg capsules (orange opaque cap printed with “WPI”and white opaque body printed with “3636”).

4 CONTRAINDICATIONS

Trospium chloride extended-release capsules are contraindicated in patients with:

- urinary retention
- gastric retention
- uncontrolled narrow-angle glaucoma
- known hypersensitivity to the drug or its ingredients. Angioedema, rash and anaphylactic reaction have been reported.

5 WARNINGS AND PRECAUTIONS

5.1 Risk of Urinary Retention

Trospium chloride extended-release capsules should be administered with caution to patients with clinically significant bladder outflow obstruction because of the risk of urinary retention [see Contraindications (4)].

5.2 Angioedema

Angioedema of the face, lips, tongue and/or larynx has been reported with trospium chloride. In one case, angioedema occurred after the first dose of trospium chloride. Angioedema associated with upper airway swelling may be life threatening. If involvement of the tongue, hypopharynx, or larynx occurs, trospium chloride should be promptly discontinued and appropriate therapy and/or measures necessary to ensure a patent airway should be promptly provided.

5.3 Decreased Gastrointestinal Motility

Trospium chloride extended-release capsules should be administered with caution to patients with gastrointestinal obstructive disorders because of the risk of gastric retention [see Contraindications (4)].Trospium chloride extended-release capsules, like other antimuscarinic agents, may decrease gastrointestinal motility and should be used with caution in patients with conditions such as ulcerative colitis, intestinal atony and myasthenia gravis.

5.4 Controlled Narrow-angle Glaucoma

In patients being treated for narrow-angle glaucoma, trospium chloride extended-release capsules should only be used if the potential benefits outweigh the risks, and in that circumstance only with careful monitoring [see Contraindications (4)].

5.5 Central Nervous System Effects

Trospium chloride extended-release capsules and trospium chloride immediate release are associated with anticholinergic central nervous system (CNS) effects [see Adverse Reactions(6.2)] . A variety of CNS anticholinergic effects have been reported, including dizziness, confusion, hallucinations and somnolence. Patients should be monitored for signs of anticholinergic CNS effects, particularly after beginning treatment or increasing the dose. Advise patients not to drive or operate heavy machinery until they know how trospium chloride extended-release capsules affect them. If a patient experiences anticholinergic CNS effects, dose reduction or drug discontinuation should be considered.

5.6 Patients with Severe Renal Impairment

Trospium chloride extended-release capsules are not recommended for use in patients with severe renal impairment (creatinine clearance less than 30 mL/minute) [see Dosage and Administration (2), Use in Specific Populations(8.6), and Clinical Pharmacology(12.3)].

5.7 Alcohol Interaction

Alcohol should not be consumed within 2 hours of trospium chloride extended-release capsules administration. In addition, patients should be informed that alcohol may enhance the drowsiness caused by anticholinergic agents.

6 ADVERSE REACTIONS

6.1 Clinical Trials Experience

Because clinical trials are conducted under widely varying conditions, the adverse reaction rates observed in the clinical trials of a drug cannot be directly compared to rates in the clinical trials of another drug and may not reflect the rates observed in clinical practice.

The data described below reflect exposure to trospium chloride extended-release capsules in 578 patients for 12 weeks in two Phase 3 double-blind, placebo controlled trials (n=1165). These studies included overactive bladder patients of ages 21 to 90 years, of which 86% were female and 85% were Caucasian. Patients received 60 mg daily doses of trospium chloride extended-release capsules. Patients in these studies were eligible to continue treatment with trospium chloride extended-release capsules 60 mg for up to one year. From both these controlled trials combined, 769 and 238 patients received treatment with trospium chloride extended-release capsules for at least 24 and 52 weeks, respectively.

There were 157 (27.2%) trospium chloride extended-release capsules patients and 98 (16.7%) placebo patients who experienced one or more double-blind treatment-emergent adverse events (TEAEs) that were assessed by the investigator as at least possibly related to study medication. The most common TEAEs were dry mouth and constipation which, when reported, commonly occurred early in treatment (often within the first week). In the two Phase 3 studies, constipation, dry mouth, and urinary retention led to discontinuation in 1%, 0.7%, and 0.5% of patients treated with trospium chloride extended-release capsules 60 mg daily, respectively. In the placebo group, there were no discontinuations due to dry mouth or urinary retention and one due to constipation.

The incidence of serious adverse events was similar among patients receiving trospium chloride extended-release capsules and patients receiving placebo. No treatment-emergent serious adverse events in either treatment group were judged by the investigators as being possibly related to the study medication.

Table 1 lists those treatment-emergent adverse events from the trials that were assessed by the investigator as possibly related to study medication, reported in at least 1% of trospium chloride extended-release capsules patients, and were more common for the trospium chloride extended-release capsules group than for placebo.

Table 1: Incidence of treatment-emergent adverse events reported in at least 1% of patients judged by the investigator as at least possibly related to treatment and more common for the trospium chloride extended-release capsules group than for placebo
 | Number of patients (%)
MedDRA Preferred term | Placebo N=587 | Trospium Chloride Extended-release Capsules N=578
Dry mouth | 22 (3.7) | 62 (10.7)
Constipation | 9 (1.5) | 49 (8.5)
Dry eye | 1 (0.2) | 9 (1.6)
Flatulence | 3 (0.5) | 9 (1.6)
Nausea | 2 (0.3) | 8 (1.4)
Abdominal pain | 2 (0.3) | 8 (1.4)
Dyspepsia | 4 (0.7) | 7 (1.2)
Urinary tract infection | 5 (0.9) | 7 (1.2)
Constipation aggravated | 3 (0.5) | 7 (1.2)
Abdominal distension | 2 (0.3) | 6 (1.0)
Nasal dryness | 0 (0.0) | 6 (1.0)

Additional adverse events reported in less than 1% of trospium chloride extended-release capsules treated patients and more common for trospium chloride extended-release capsules than placebo, judged by the investigator at least possibly related to treatment were: vision blurred, feces hard, back pain, somnolence, urinary retention, and dry skin.

Table 2 lists all treatment-emergent adverse events for the trials reported in at least 2% of all trospium chloride extended-release capsules patients and more common for the trospium chloride extended-release capsules group than for placebo without regard to the investigator’s judgment on drug relatedness.

Table 2: Incidence of treatment-emergent adverse events reported in at least 2% of patients regardless of reported relationship to treatment and more common for the trospium chloride extended-release capsules group than for placebo
 | Number of patients (%)
MedDRA Preferred term | Placebo N=587 | Trospium Chloride Extended-release Capsules N=578
Dry mouth | 22 (3.7) | 64 (11.1)
Constipation | 10 (1.7) | 52 (9.0)
Urinary tract infection | 29 (4.9) | 42 (7.3)
Nasopharyngitis | 10 (1.7) | 17 (2.9)
Influenza | 9 (1.5) | 13 (2.2)

Additional adverse events reported in less than 2% of trospium chloride extended-release capsules treated patients and twice as frequent for trospium chloride extended-release capsules compared to placebo, regardless of reported relationship to treatment were: tachycardia, dry eyes, abdominal pain, dyspepsia, abdominal distension, constipation aggravated, nasal dryness, and rash.

In the open-label treatment phase, the most common TEAEs reported in the 769 patients with at least 6 months exposure to trospium chloride extended-release capsules were: constipation, and dry mouth. Urinary tract infection and rash was also reported in several patients, including one of each judged by the investigator to be possibly related to treatment. Several adverse events were reported as severe in the open-label treatment phase, including one urinary tract infection, two urinary retention events, and one aggravated constipation.

6.2 Post-marketing Experience

The following adverse reactions have been identified during post-approval use of trospium chloride. Because these reactions are reported voluntarily from a population of uncertain size, it is not always possible to reliably estimate their frequency or establish a causal relationship to drug exposure.

Gastrointestinal – gastritis; Cardiovascular – palpitations, supraventricular tachycardia, chest pain, syncope, “hypertensive crisis”; Immunological – Stevens-Johnson syndrome, anaphylactic reaction, angioedema; Nervous System – dizziness, confusion, vision abnormal, hallucinations, somnolence, and delirium; Musculoskeletal – rhabdomyolysis; General – rash.

7 DRUG INTERACTIONS

Trospium is metabolized by ester hydrolysis and excreted by the kidneys through a combination of tubular secretion and glomerular filtration. Based on in vitrodata, no clinically relevant metabolic drug-drug interactions are anticipated with trospium. However, some drugs which are actively secreted by the kidney may interact with trospium by competing for renal tubular secretion.

The concomitant use of trospium chloride extended-release capsules with other antimuscarinic agents that produce dry mouth, constipation, and other anticholinergic effects may increase the frequency and/or severity of such effects. Trospium chloride extended-release capsules may potentially alter the absorption of some concomitantly administered drugs due to anticholinergic effects on gastrointestinal motility.

7.1 Digoxin

Concomitant use of trospium chloride 20 mg twice daily and digoxin did not affect the pharmacokinetics of either drug [ see Clinical Pharmacology (12.3)] .

7.2 Antacid

While the systemic exposure of trospium on average was comparable with and without antacid containing aluminum hydroxide and magnesium carbonate, 5 out of 11 individuals in a drug interaction study demonstrated either an increase or decrease in trospium exposure, in presence of antacid. The clinical relevance of these findings is not known [ see Clinical Pharmacology (12.3)] .

7.3 Metformin

Co-administration of 500 mg metformin immediate release tablets twice daily reduced the steady-state systemic exposure of trospium by approximately 29% for mean AUC0-24and by 34% for mean Cmax.The effect of a decrease in trospium exposure on the efficacy of trospium chloride extended-release capsules is unknown. The steady-state pharmacokinetics of metformin were comparable when administered with or without 60 mg trospium chloride extended-release capsules once daily under fasted condition. The effect of metformin at higher doses on trospium PK is unknown [ see Clinical Pharmacology (12.3)] .

8 USE IN SPECIFIC POPULATIONS

8.1 Pregnancy

Teratogenic Effects
Pregnancy Category C: There are no adequate and well-controlled studies of trospium chloride extended-release capsules in pregnant women. Trospium chloride extended-release capsules should be used during pregnancy only if the potential benefit to the patient outweighs the risk to the patient and fetus. Women who become pregnant during trospium chloride extended-release capsules treatment are encouraged to contact their physician.

Trospium chloride was not teratogenic at statistically significant levels in rats or rabbits administered doses up to 200 mg/kg/day. This corresponds to systemic exposures up to approximately 16 and 32 times, respectively (based on AUC), the clinical exposure at the maximum recommended human dose (MRHD) of 60 mg. However, in rabbits, one fetus in each of the three treated dose groups (1, 1, and 32 times the MRHD) demonstrated multiple malformations, including umbilical hernia and skeletal malformations. A no effect level for maternal and fetal toxicity was observed at levels approximately equivalent to the clinical exposure at the MRHD (20 mg/kg/day in rats and rabbits). No developmental toxicity was observed in the offspring of female rats exposed pre- and post-natally to up to 200 mg/kg/day.

8.2 Labor and Delivery

The effect of trospium chloride extended-release capsules on labor and delivery is unknown.

8.3 Nursing Mothers

Trospium chloride (2 mg/kg orally and 50 mcg/kg intravenously) was excreted, to a limited extent (less than 1%), into the milk of lactating rats (primarily as parent compound). It is not known whether this drug is excreted into human milk. Because many drugs are excreted into human milk, trospium chloride extended-release capsules should be used during lactation only if the potential benefit justifies the potential risk.

8.4 Pediatric Use

The safety and effectiveness of trospium chloride extended-release capsules in pediatric patients have not been established.

8.5 Geriatric Use

Of 1165 patients in Phase 3 clinical studies of trospium chloride extended-release capsules, 37% (n=428) were ages 65 and over, while 12% (n=143) were ages 75 and over.

No overall differences in effectiveness were observed between those subjects aged 65 and over and younger subjects. In trospium chloride extended-release capsules subjects ages 65 and over compared to younger subjects, the following adverse reactions were reported at a higher incidence: dry mouth, constipation, abdominal pain, dyspepsia, urinary tract infection and urinary retention. In subjects ages 75 and over, three reported a fall and in one of them a relationship to the event could not be excluded.

8.6 Renal Impairment

Severe renal impairment (creatinine clearance less than 30 mL/minute) may significantly alter the disposition of trospium chloride extended-release capsules. In a study of immediate-release trospium chloride, 4.2-fold and 1.8-fold increases in mean AUC(0-∞)and Cmax,respectively, were detected in patients with severe renal impairment. Use of trospium chloride extended-release capsules is not recommended in patients with severe renal impairment [ see Warnings and Precautions(5.4) and Clinical Pharmacology(12.3)] . The pharmacokinetics of trospium chloride have not been studied in patients with creatinine clearance ranging from 30 to 80 mL/min.

Trospium is known to be substantially excreted by the kidney, and the risk of adverse reactions may be greater in patients with impaired renal function.

8.7 Hepatic Impairment

There is no information regarding the effect of severe hepatic impairment on exposure to trospium chloride extended-release capsules. In a study of patients with mild and with moderate hepatic impairment, given 40 mg of immediate-release trospium chloride, mean Cmaxincreased 12% and 63%, respectively, and mean AUC(0-∞)decreased 5% and 15%, respectively, compared to healthy subjects. The clinical significance of these findings is unknown. Caution is advised, however, when administering trospium chloride extended-release capsules to patients with moderate to severe hepatic impairment.

10 OVERDOSAGE

Overdosage with antimuscarinic agents, including trospium chloride extended-release capsules, can result in severe antimuscarinic effects. Supportive treatment should be provided according to symptoms. In the event of overdosage, ECG monitoring is recommended.

11 DESCRIPTION

Trospium chloride extended-release capsules are an extended-release formulation of trospium chloride, a quaternary ammonium compound with the chemical name of Spiro[8-azoniabicyclo[3.2.1]octane-8,1'-pyrrolidinium], 3-[(hydroxydiphenylacetyl)oxy]-, chloride, (1α, 3β, 5α). The empirical formula of trospium chloride is C25H30ClNO3and its molecular weight is 427.97. The structural formula of trospium chloride is represented below:

Trospium chloride is a fine, colorless to slightly yellow, crystalline solid. The compound’s solubility in water is approximately 1 g/2 mL.

Trospium chloride extended-release capsules contain 60 mg of trospium chloride, a muscarinic antagonist, for oral administration. Each capsule also contains the following inactive ingredients:corn starch, ethylcellulose, hypromellose, methacrylic acid copolymer, polyethylene glycol, polysorbate 80, polyvinyl alcohol, sodium lauryl sulfate, sucrose, talc, titanium dioxide and triethyl citrate. The capsule shell and imprinting ink have the following inactive ingredients: D&C Red #28, D&C Yellow # 10, FD&C Blue # 1, FD&C Blue # 2, FD&C Red #40, FDA/E172 Yellow iron oxide, gelatin, iron oxide black, propylene glycol, shellac glaze, and titanium dioxide.

12 CLINICAL PHARMACOLOGY

12.1 Mechanism of Action

Trospium chloride is an antispasmodic, antimuscarinic agent.

Trospium chloride antagonizes the effect of acetylcholine on muscarinic receptors in cholinergically innervated organs including the bladder. Its parasympatholytic action reduces the tonus of smooth muscle in the bladder.

In vitroreceptor binding studies have demonstrated the selectivity of trospium chloride for muscarinic over nicotinic receptors, and similar affinity for the M2and M3muscarinic receptor subtypes. M2and M3receptors are found in the bladder and may play a role in the pathogenesis of overactive bladder.

12.2 Pharmacodynamics

Placebo-controlled studies assessing the impact on urodynamic variables of an immediate-release formulation of trospium chloride were conducted in patients with conditions characterized by involuntary detrusor contractions. The results demonstrated that trospium chloride increases maximum cystometric bladder capacity and volume at first detrusor contraction.

Electrophysiology
The effect of 20 mg twice daily and up to 100 mg twice daily of an immediate-release formulation of trospium chloride on QT interval was evaluated in a single-blind, randomized, placebo and active (moxifloxacin 400 mg daily) controlled, 5-day parallel trial in 170 male and female healthy volunteer subjects aged 18 to 45 years. The QT interval was measured over a 24-hour period at steady state. Trospium chloride was not associated with an increase in individual corrected (QTcI) or Fridericia corrected (QTcF) QT interval at any time during steady state measurement, while moxifloxacin was associated with a 6.4 msec increase in QTcF.

In this study, asymptomatic, non-specific T-wave inversions were observed more often in subjects receiving trospium chloride than in subjects receiving moxifloxacin or placebo following five days of treatment. The clinical significance of T-wave inversion in this study is unknown. This finding was not observed during routine safety monitoring in overactive bladder patients from 2 placebo-controlled clinical trials in 591 patients treated with 20 mg twice daily of immediate-release trospium chloride, nor was it observed in 2 placebo-controlled clinical trials in 578 patients treated with trospium chloride extended-release capsules.

Also in this study, the immediate-release formulation of trospium chloride was associated with an increase in heart rate that correlated with increasing plasma concentration, with a mean elevation in heart rate compared to placebo of 9 beats per minute for the 20 mg dose and of 18 beats per minute for the 100 mg dose. In the two Phase 3 trospium chloride extended-release capsules trials the mean increase in heart rate compared to placebo was approximately 3 beats per minute in both studies.

12.3 Pharmacokinetics

Absorption: Mean absolute bioavailability of a 20 mg immediate-release dose is 9.6% (range 4.0 to 16.1%). Following a single 60 mg dose of trospium chloride extended-release capsules, peak plasma concentration (Cmax) of 2.0 ng/mL occurred 5.0 hours post dose. By contrast, following a single 20 mg dose of an immediate-release formulation of trospium chloride, Cmaxwas 2.7 ng/mL.

Effect of Food:Administration of trospium chloride extended-release capsules immediately after a high (50%) fat-content meal reduced the oral bioavailability of trospium chloride by 35% for AUC(0-Tlast)and by 60% for Cmax.Other pharmacokinetic parameters such as Tmaxand t1/2were unchanged in the presence of food.

A summary of mean (± standard deviation) pharmacokinetic parameters for a single dose of 60 mg trospium chloride extended-release capsules is provided in Table 3.

Table 3: Mean (±SD) Pharmacokinetic Parameter Estimates for a Single 60 mg Oral Dose of Trospium Chloride Extended-release Capsules in Healthy Volunteers
Treatment | AUC(0-24) (ng●h/mL) | Cmax (ng/mL) | Tmaxa (h) | t1/2b (h)
Trospium Chloride Extended-release Capsules 60 mg | 18.0 ± 13.4 | 2.0 ± 1.5 | 5.0 (3.0 to 7.5) | 36 ± 22
aTmaxexpressed as median (range).
bt1/2was determined following multiple (10) doses.

The mean sample concentration-time (+ standard deviation) profile for trospium chloride extended-release capsules is shown in Figure 1.

Administration of trospium chloride extended-release capsules immediately after a high (50%) fat-content meal reduced the oral bioavailability of trospium chloride by 35% for AUC(0-Tlast)and by 60% for Cmax.Other pharmacokinetic parameters such as Tmaxand t1/2were unchanged in the presence of food. Coadministration with antacid had inconsistent effects on the oral bioavailability of trospium chloride extended-release capsules.

Distribution:Protein binding ranged from 50 to 85%, depending upon the assessment method used, when a range of concentration levels of trospium chloride (0.5 to 50 mcg/L) were incubated in vitrowith human serum.

The ratio of^3H-trospium chloride in plasma to whole blood was 1.6:1. This ratio indicates that the majority of^3H- trospium chloride is distributed in plasma.

Trospium chloride is widely distributed, with an apparent volume of distribution >600 L.

Metabolism:The metabolic pathway of trospium in humans has not been fully defined. Of the dose absorbed following oral administration, metabolites account for approximately 40% of the excreted dose. The major metabolic pathway of trospium is hypothesized as ester hydrolysis with subsequent conjugation of benzylic acid to form azoniaspironortropanol with glucuronic acid. CYP P450 does not contribute significantly to the elimination of trospium. Data taken from in vitrostudies of human liver microsomes, investigating the inhibitory effect of trospium on seven CYP P450 isoenzyme substrates (CYP1A2, 2A6, 2C9, 2C19, 2D6, 2E1, and 3A4), suggest a lack of inhibition at clinically relevant concentrations.

Excretion:The plasma half-life for trospium following oral administration of trospium chloride extended-release capsules is approximately 35 hours. After oral administration of an immediate-release formulation of^14C-labeled trospium chloride, a majority of the dose (85.2%) was recovered in feces and a smaller amount (5.8% of the dose) was recovered in urine. Of the radioactivity excreted into the urine, 60% was unchanged trospium.

The mean renal clearance for trospium (29.07 L/hour) is 4-fold higher than average glomerular filtration rate, indicating that active tubular secretion is a major route of elimination. There may be competition for elimination with other compounds that are also renally eliminated [see Drug Interactions (7) ].

Drug Interactions

Digoxin: Concomitant use of 20 mg trospium chloride immediate release twice daily at steady state and a single dose of 0.5 mg digoxin in a crossover study with 40 male and female subjects did not affect the pharmacokinetics of either drug.

Antacid: A drug interaction study was conducted to evaluate the effect of an antacid containing aluminum hydroxide and magnesium carbonate on the pharmacokinetics of trospium chloride extended-release capsules (n=11). While the systemic exposure of trospium on average was comparable with and without antacid, 5 individuals demonstrated either an increase or decrease in trospium exposure, in presence of antacid.

Metformin: A drug interaction study was conducted in which trospium chloride extended-release capsules 60 mg once daily was co-administered with Glucophage ®(metformin hydrochloride) 500 mg twice daily under steady-state conditions in 44 healthy subjects. Co-administration of 500 mg metformin immediate release tablets twice daily reduced the steady-state systemic exposure of trospium by approximately 29% for mean AUC0-24and by 34% for mean Cmax.The effect of decrease in trospium exposure on the efficacy of trospium chloride extended-release capsules is unknown.The steady-state pharmacokinetics of metformin were comparable when administered with or without 60 mg trospium chloride extended-release capsules once daily under fasted condition. The effect of metformin at higher doses on trospium PK is unknown.

Specific Populations

Age:In a phase 3 clinical trial of trospium chloride extended-release capsules, the observed plasma trospium concentrations were similar in older (greater than or equal to 65 years) and younger (less than 65 years) OAB patients.

Pediatric:The pharmacokinetics of trospium chloride extended-release capsules were not evaluated in pediatric patients.

Race:Pharmacokinetic differences due to race have not been studied.

Gender:Gender differences in pharmacokinetics of trospium chloride extended-release capsules have not been formally assessed. Data from healthy subjects suggests lower exposure in males compared to females.

Hepatic Impairment:There is no information regarding the effect of severe hepatic impairment on exposure to trospium chloride extended-release capsules. In a study of patients with mild (Child-Pugh score 5 to 6) and with moderate (Child-Pugh score 7 to 8) hepatic impairment, given 40 mg of immediate-release trospium chloride, mean Cmaxincreased 12% and 63% respectively, and mean AUC(0-∞)decreased 5% and 15%, respectively, compared to healthy subjects.

Renal Impairment:The pharmacokinetics of trospium chloride extended-release capsules in patients with severe renal impairment has not been evaluated. In a study of an immediate-release formulation of trospium chloride, 4.2-fold and 1.8-fold increases in mean AUC(0-∞)and Cmax, respectively, were detected in patients with severe renal impairment (creatinine clearance less than 30 mL/minute), compared with healthy subjects, along with the appearance of an additional elimination phase with a long half-life (~33 hours vs. 18 hours). Use of trospium chloride extended-release capsules is not recommended in patients with severe renal impairment [see Dosage and Administration (2) ]. The pharmacokinetics of trospium chloride have not been studied in people with creatinine clearance ranging from 30 to 80 mL/min.

13 NONCLINICAL TOXICOLOGY

13.1 Carcinogenesis, Mutagenesis, Impairment of Fertility

Carcinogenesis:Carcinogenicity studies with trospium chloride were conducted in mice and rats for 78 weeks and 104 weeks, respectively, at maximally tolerated doses. No evidence of a carcinogenic effect was found in either mice or rats administered up to 200 mg/kg/day (approximately 1 and 16 times, respectively (based on AUC), the expected clinical exposure levels at the maximum recommended human dose (MRHD) of 60 mg.

Mutagenesis:Trospium chloride was not mutagenic nor genotoxic in tests in vitroin bacteria (Ames test) and mammalian cells (L5178Y mouse lymphoma and CHO cells) or in vivoin the mouse micronucleus test.

Impairment of Fertility:No evidence of impaired fertility was observed in rats administered doses up to 200 mg/kg/day (about 16 times the expected clinical exposure at the MRHD, based on AUC).

14 CLINICAL STUDIES

Trospium chloride extended-release capsules were evaluated for the treatment of patients with overactive bladder who had symptoms of urinary frequency, urgency and urge urinary incontinence in two 12-week, randomized, double-blind, placebo-controlled studies. For both studies, entry criteria required the presence of urge incontinence (predominance of urge), at least one incontinence episode per day, and 10 or more micturitions (voids) per day (assessed by 3-day urinary diary). Medical history and data from the baseline urinary diary confirmed the diagnosis. Approximately 88% of the patients enrolled completed the 12-week studies. The mean age was 60 years, and the majority of patients were female (84%) and Caucasian (86%).

The co-primary endpoints in the trials were the mean change from baseline to Week 12 in number of voids/24 hours (reductions in urinary frequency) and the mean change from baseline to Week 12 in number of incontinence episodes/24 hours. Secondary endpoints included mean change from baseline to Week 12 in volume per void.

Study 1 included 592 patients in both trospium chloride extended-release capsules 60 mg and placebo groups. As illustrated in Table 4 and Figures 2 and 3, trospium chloride extended-release capsules demonstrated statistically significantly (p<0.01) greater reductions in the urinary frequency and incontinence episodes, and increases in void volume when compared to placebo starting at Week 1 and maintained through Weeks 4 and 12.

Table 4: Mean (SE) Change from Baseline in Urinary Frequency, Urge Incontinence Episodes and Void Volume in Study 1
Efficacy Endpointa | Week | Placebo | Trospium Chloride Extended-release Capsules | P-Value
Urinary frequency /24 hours |  | (N=300) | (N=292)
Mean Baseline | 0 | 12.7 (0.2) | 12.8 (0.2)
Mean Change from Baseline | 1 | - 1.2 (0.1) | - 1.7 (0.1) | 0.0092
 | 4 | - 1.6 (0.2) | - 2.4 (0.2) | <0.0001
 | 12 | - 2.0 (0.2) | - 2.8 (0.2) | <0.0001
Urge incontinence episodes / week |  | (N=300) | (N=292)
Mean Baseline | 0 | 29.0 (1.3) | 28.8 (1.3)
Mean Change from Baseline | 1 | - 8.7 (1.0) | - 13.0 (0.9) | 0.0003
 | 4 | - 12.2 (1.1) | - 16.5 (1.2) | 0.0054
 | 12 | - 13.5 (1.1) | - 17.3 (1.2) | 0.0024
Urinary volume / void (mL) |  | (N=300) | (N=290)
Mean Baseline | 0 | 155.9 (3.0) | 151.0 (2.9)
Mean Change from Baseline | 1 | 12.1 (2.1) | 21.6 (2.8) | 0.0036
 | 4 | 17.2 (2.5) | 30.0 (3.1) | 0.0007
 | 12 | 18.9 (2.8) | 29.8 (3.2) | 0.0039
atreatment differences assessed by rank ANOVA for intent-to-treat population, last observation carried forward (ITT:LOCF) data set

Study 2 included 543 patients in both trospium chloride extended-release capsules 60 mg and placebo groups and was identical in design to Study 1. As illustrated in Table 5 and Figures 4 and 5, trospium chloride extended-release capsules demonstrated statistically significantly (p<0.01) greater reductions in urinary frequency and incontinence episodes, and increases in void volume when compared to placebo at Weeks 4 and 12. However, at Week 1, statistically significant reductions were seen in urinary incontinence episodes and volume void only.

Table 5: Mean (SE) Change from Baseline in Urinary Frequency, Urge Incontinence Episodes and Void Volume in Study 2
Efficacy Endpointa | Week | Placebo | Trospium Chloride Extended-release Capsules | P-Value
Urinary Frequency /24 hours |  | (N=276) | (N=267)
Mean Baseline | 0 | 12.9 (0.2) | 12.8 (0.2)
Mean Change from Baseline | 1 | - 1.2 (0.2) | - 1.4 (0.2) | 0.0759
 | 4 | - 1.7 (0.2) | - 2.3 (0.2) | 0.0047
 | 12 | - 1.8 (0.2) | - 2.5 (0.2) | 0.0009
Urge incontinence episodes / week |  | (N=276) | (N=267)
Mean Baseline | 0 | 28.3 (1.4) | 28.2 (1.2)
Mean Change from Baseline | 1 | - 7.3 (1.0) | - 11.9 (1.0) | <0.0001
 | 4 | - 10.6 (1.1) | - 15.8 (1.1) | <0.0001
 | 12 | - 11.3 (1.2) | - 16.4 (1.3) | <0.0001
Urinary volume / void (mL) |  | (N=276) | (N=266)
Mean Baseline | 0 | 151.8 (2.8) | 149.6 (2.9)
Mean Change from Baseline | 1 | 11.9 (2.5) | 24.1 (2.4) | <0.0001
 | 4 | 19.6 (3.1) | 29.3 (3.0) | 0.0020
 | 12 | 17.8 (3.3) | 31.5 (3.4) | 0.0014
atreatment differences assessed by rank ANOVA for intent-to-treat population, last observation carried forward (ITT:LOCF) data set

16 HOW SUPPLIED/STORAGE AND HANDLING

Trospium chloride extended-release capsules are supplied as 60 mg capsules (orange cap printed with “WPI”and white opaque body printed with “3636”):
60 mg capsule, 30 count, HDPE bottle: NDC 60429-098-30

Store at 20° to 25°C (68° to 77°F) [See USP Controlled Room Temperature].

17 PATIENT COUNSELING INFORMATION

“See FDA-Approved Patient Labeling (Patient Information)”

17.1 Angioedema

Patients should be informed that trospium chloride extended-release capsules may produce angioedema which could result in life-threatening airway obstruction. Patients should be advised to promptly discontinue trospium chloride extended-release capsules therapy and seek immediate medical attention if they experience edema of the tongue, edema of the laryngopharynx, or difficulty breathing.

17.2 When Not to Use

Prior to treatment, patients should fully understand the risks and benefits of trospium chloride extended-release capsules. In particular, patients should be informed not to take trospium chloride extended-release capsules if they:

- have urinary retention;
- gastric retention;
- uncontrolled narrow-angle glaucoma;
- are allergic to any component of trospium chloride extended-release capsules .

17.3 Administration

Patients should be instructed regarding the recommended dosing and administration of trospium chloride extended-release capsules:

- Take one trospium chloride extended-release capsule daily in the morning with water.
- Take trospium chloride extended-release capsule on an empty stomach or at least 1 hour before a meal.
- Use of alcoholic beverages within 2 hours of dosing with trospium chloride extended-release capsule is not recommended.

17.4 Adverse Reactions

Patients should be informed that the most common side effects with trospium chloride extended-release capsules are dry mouth and constipation and that other less common side effects include trouble emptying the bladder, blurred vision, and heat prostration. Because anticholinergics, such as trospium chloride extended-release capsules, may produce dizziness or blurred vision, patients should be advised to exercise caution in decisions to engage in potentially dangerous activities until the drug’s effects have been determined. Patients should be informed that alcohol may enhance the drowsiness caused by anticholinergic agents.

Patient Information

Trospium (TROSE-pee-um) Chloride Extended-release Capsules

Read the Patient Information that comes with trospium chloride extended-release capsules before you start taking it and each time you get a refill. There may be new information. This leaflet does not take the place of talking with your doctor about your medical condition or your treatment.

What aretrospium chloride extended-release capsules?

Trospium chloride extended-release capsules are a prescription medicine used to treat adults with overactive bladder who have the following symptoms:

- a strong need to urinate right away;
- leaking or wetting accidents due to a strong need to urinate right away;
- a need to urinate often.

Who should not taketrospium chloride extended-release capsules?

Do not take trospium chloride extended-release capsules if you:

- have trouble emptying your bladder;
- have delayed or slow emptying of your stomach;
- have an eye problem called “uncontrolled narrow-angle glaucoma”;
- are allergic to trospium chloride extended-release capsules or any of its ingredients. See the end of this leaflet for a complete list of ingredients.

Trospium chloride extended-release capsules have not been studied in children under the age of 18 years.

What should I tell my doctor before startingtrospium chloride extended-release capsules?

Tell your doctor about all of your medical conditions including if you:

- have any stomach or intestinal problems or problems with constipation;
- have trouble emptying your bladder or have a weak urine stream;
- have an eye problem called narrow-angle glaucoma;
- have kidney problems;
- have liver problems;
- are pregnant or planning to become pregnant. It is not known if trospium chloride extended-release capsules can harm your unborn baby.
- are breastfeeding. It is not known if trospium passes into breast milk and if it can harm your baby. You should talk to your doctor about the best way to feed your baby if you are taking trospium chloride extended-release capsules.

Tell your doctor about all the medicines you take including prescription and nonprescription medicines, vitamins and herbal supplements. Trospium chloride extended-release capsules and certain other medicines can interact and make some side effects worse. Trospium chloride extended-release capsules can affect how other medicines are handled by the body.

Know all the medicines you take. Keep a list of them with you to show your doctor and pharmacist each time you get a new medicine.

How should I taketrospium chloride extended-release capsules?

Take trospium chloride extended-release capsules exactly as prescribed.

- Take one trospium chloride extended-release capsule daily in the morning with water.
- Take trospium chloride extended-release capsule on an empty stomach or at least 1 hour before a meal.
- Do not take alcohol within 2 hours of taking trospium chloride extended-release capsule.
- If you take too much trospium chloride extended-release capsules, call your local Poison Control Center or go to an emergency room right away.

What are the possible side effects oftrospium chloride extended-release capsules?

Trospium chloride extended-release capsules may cause allergic reactions that may be serious. Symptoms of a serious allergic reaction may include swelling of the face, lips, throat or tongue. If you experience these symptoms, you should stop taking trospium chloride extended-release capsules and get emergency medical help right away.

The most common side effects with trospium chloride extended-release capsules are:

- dry mouth;
- constipation.

Trospium chloride extended-release capsules may cause other less common side effects, including:

- trouble emptying the bladder;
- blurred vision and drowsiness. Do not drive or operate heavy machinery until you know how trospium chloride extended-release capsules affect you.
- heat prostration. Due to decreased sweating, heat prostration can occur when drugs such as trospium chloride extended-release capsules are used in a hot environment.

Tell your doctor if you have any side effects that bother you or that do not go away.

These are not all possible side effects of trospium chloride extended-release capsules. For more information, ask your doctor, healthcare professional or pharmacist.

How should I storetrospium chloride extended-release capsules?

- Keep trospium chloride extended-release capsules and all other medicines out of the reach of children.
- Store trospium chloride extended-release capsules at 20° to 25°C (68° to 77°F) [See USP Controlled Room Temperature].
- Safely dispose of trospium chloride extended-release capsules that are out of date or that you no longer need.

General information abouttrospium chloride extended-release capsules

Medicines are sometimes prescribed for conditions that are not mentioned in patient information leaflets. Do not use trospium chloride extended-release capsules for a condition for which it was not prescribed. Do not give trospium chloride extended-release capsules to other people, even if they have the same symptoms you have. It may harm them.

This leaflet summarizes the most important information about trospium chloride extended-release capsules. If you would like more information, talk with your doctor. You can ask your doctor or pharmacist for information about trospium chloride extended-release capsules that is written for health professionals. You can also call Actavis’s product information department at 1-800-272-5525 or visit the website at www.actavis.com.

What are the ingredients introspium chloride extended-release capsules?

Active Ingredient: trospium chloride.
Inactive Ingredients:corn starch, ethylcellulose, hypromellose, methacrylic acid copolymer, polyethylene glycol, polysorbate 80, polyvinyl alcohol, sodium lauryl sulfate, sucrose, talc, titanium dioxide and triethyl citrate. The capsule shell and imprinting ink have the following inactive ingredients: D&C Red #28, D&C Yellow # 10, FD&C Blue # 1, FD&C Blue # 2, FD&C Red #40, FDA/E172 Yellow iron oxide, gelatin, iron oxide black, propylene glycol, shellac glaze, and titanium dioxide.

Glucophage ®is a registered trademark of Merck Santé S.A.S.

Manufactured by:
Actavis Laboratories, FL., Inc.
Fort Lauderdale, FL 33314 USA

Distributed by:
Actavis Pharma, Inc .
Parsippany, NJ 07054 USA

Revised: August 2014 174696-3

Marketed by:
GSMS, Inc.
Camarillo, CA 93012 USA

PACKAGE LABEL

PRINCIPAL DISPLAY PANEL

NDC 60429-098-30
Once-Daily
Trospium Chloride
Extended-release
Capsules
60 mg
Actavis 30 Capsules Rx only